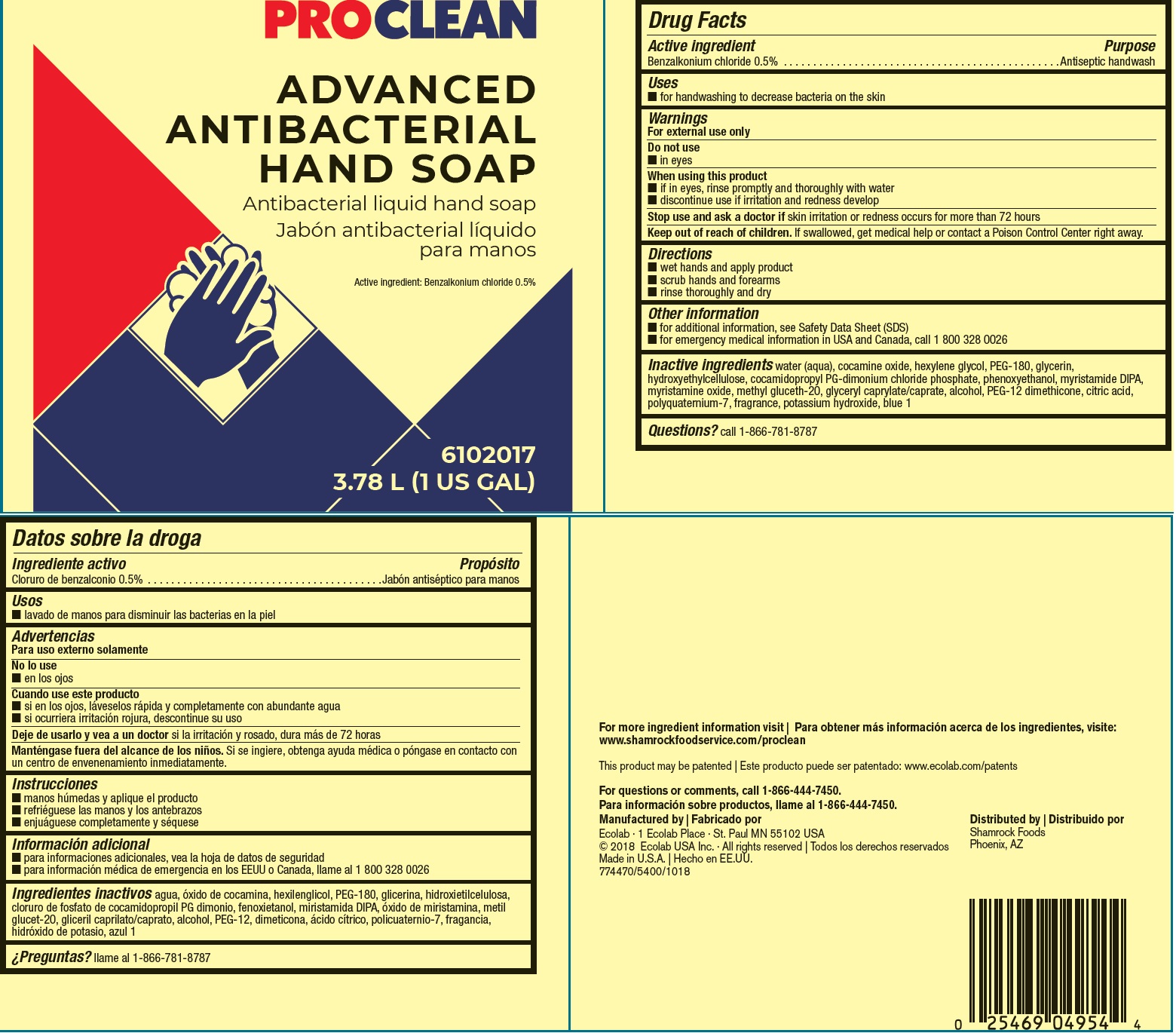 DRUG LABEL: PROCLEAN
NDC: 47593-602 | Form: SOLUTION
Manufacturer: Ecolab Inc.
Category: otc | Type: HUMAN OTC DRUG LABEL
Date: 20240805

ACTIVE INGREDIENTS: BENZALKONIUM CHLORIDE 5 mg/1 mL
INACTIVE INGREDIENTS: WATER; COCAMINE OXIDE; HEXYLENE GLYCOL; POLYETHYLENE GLYCOL 8000; GLYCERIN; HYDROXYETHYL CELLULOSE (4000 MPA.S AT 1%); COCAMIDOPROPYL PROPYLENE GLYCOL-DIMONIUM CHLORIDE PHOSPHATE; PHENOXYETHANOL; MYRISTIC DIISOPROPANOLAMIDE; MYRISTAMINE OXIDE; METHYL GLUCETH-20; GLYCERYL MONO- AND DICAPRYLOCAPRATE; ALCOHOL; PEG-12 DIMETHICONE; ANHYDROUS CITRIC ACID; POLYQUATERNIUM-7 (70/30 ACRYLAMIDE/DADMAC; 1600000 MW); POTASSIUM HYDROXIDE; FD&C BLUE NO. 1

Drug Facts

Active Ingredient

Benzalkonium chloride 0.5%

Purpose

Antiseptic handwash

Uses

- for handwashing to decrease bacteria on the skin

Warning

For external use only

Do not use

- in eyes

When using the product

- if in eyes, rinse promptly and thoroughly with water
- discontinue use if irritation and redness develop

Stop use and ask a physician if skin irritation or redness occurs for more than 72 hours

Keep out of reach of children. If swallowed, get medical help or contact a Poison Control Center right away.

Directions

- wet hands and apply foam
- scrub hands and forearms
- rinse thoroughly and dry

Other information

- for additional information, see Safety Data Sheet (SDS)
- for emergency medical information, in USA and Canada, call 1 800 328 0026

INACTIVE INGREDIENT

Inactive ingredients water (aqua), cocamine oxide, hexylene glycol, PEG-180, glycerin, hydroxyethylcellulose, cocamidopropyl PG-dimonium chloride phosphate, phenoxyethanol, myristamide DIPA, myristamine oxide, methyl gluceth-20, glyceryl caprylate/caprate, alcohol, PEG-12 dimethicone, citric acid, polyquaternium-7, fragrance, potassium hydroxide, blue 1

Questions? call 1-866-781-8787

Representative Label and Principal Display Panel

PROCLEAN

ADVANCED

ANTIBACTERIAL

HAND SOAP

Antibacterial liquid hand soap

Active ingredient: Benzalkonim chloride 0.5%

6102017

3.78 L (1 US GAL)

For more ingredient information visit: www.shamrockfoodservice.com/proclean

This product may be patented

For questions or comments, call 1-866-444-7450.

Manufactured by

Ecolab · 1 Ecolab Place · St. Paul MN 55102 USA

© 2018 Ecolab USA Inc. · All rights reserved

774470/5400/1018

Distributed by Shamrock Foods

Phoenix, AZ